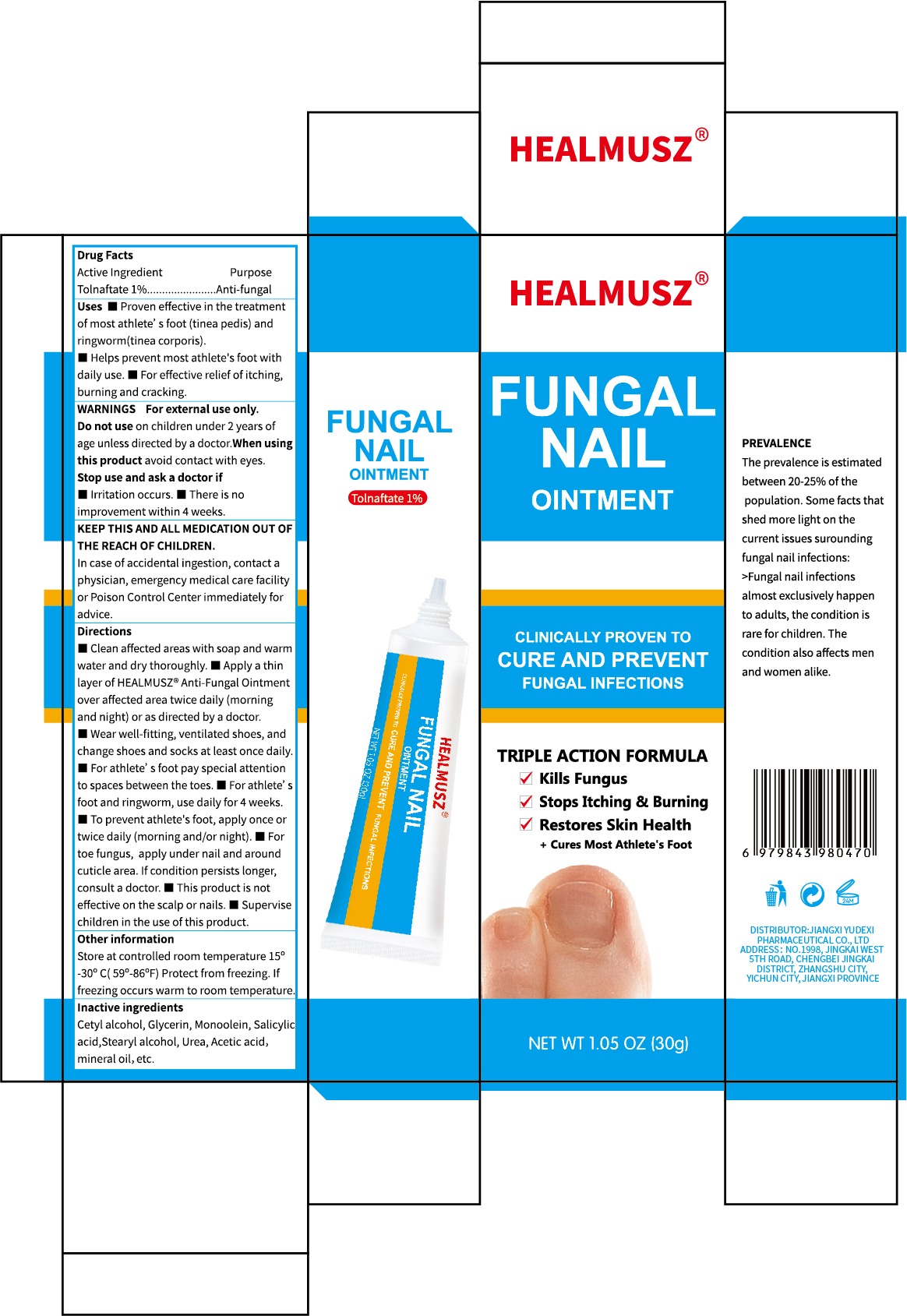 DRUG LABEL: HEALMUSZ FUNGAL NAIL
NDC: 85248-056 | Form: OINTMENT
Manufacturer: Jiangxi Yudexi Pharmaceutical Co., LTD
Category: otc | Type: HUMAN OTC DRUG LABEL
Date: 20260206

ACTIVE INGREDIENTS: TOLNAFTATE 1 g/100 g
INACTIVE INGREDIENTS: GLYCERYL MONOOLEATE; SALICYLIC ACID; UREA; MINERAL OIL; ACETIC ACID; GLYCERIN; STEARYL ALCOHOL

85248-056

Active Ingredient

Tolnaftate 1%.

Purpose

Anti-fungal

Use

■Proven effective in the treatment of most athlete' s foot (tinea pedis) and ringworm(tinea corporis).
■Helps prevent most athlete's foot with daily use. ■For effective relief of itching,burning and cracking.

Warnings

Forexternal use only

Do not use

on children under 2 yearsof age unless directed by a doctor

When Using

avoid contact witheyes

Stop Use

■Irritation occurs. ■There is no improvement within 4 weeks.

Ask Doctor

■Irritation occurs. ■There is no improvement within 4 weeks.

Keep Oot Of Reach Of Children

In case of accidental ingestion, contact a physician, emergency medical care facility or Poison Control Centerimmediately for advice.

Directions

■Clean affected areas with soap and warm water and dry thoroughly. ■ Apply a thin layer of HEALMUSZ Anti-Fungal Ointment over affected area twice daily (morning and night) or as directed by a doctor.■Wear well-fitting, ventilated shoes, and change shoes and socks at least once daily.■For athlete' s foot pay special attention to spaces between the toes. ■For athlete's foot and ringworm, use daily for 4 weeks.■To prevent athlete's foot, apply once or twice daily (morning and/or night). For toe fungus, apply under nail and around cuticle area. If condition persists longer,consult a doctor. ■ This product is not effective on the scalp or nails. ■Supervise children in the use of this product.

Other information

Store at controlled room temperature 15°-30℃(59°-86°F) Protect from freezing.If freezing occurs warm to room temperature.

Inactive ingredients

Cetyl alcohol,Glycerin, Monoolein, Salicylic acid,Stearyl alcohol, Urea, Acetic acid,mineral oil, etc.